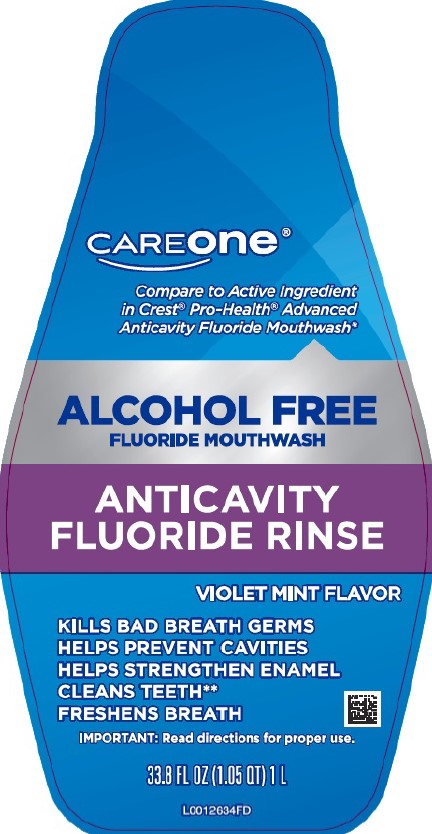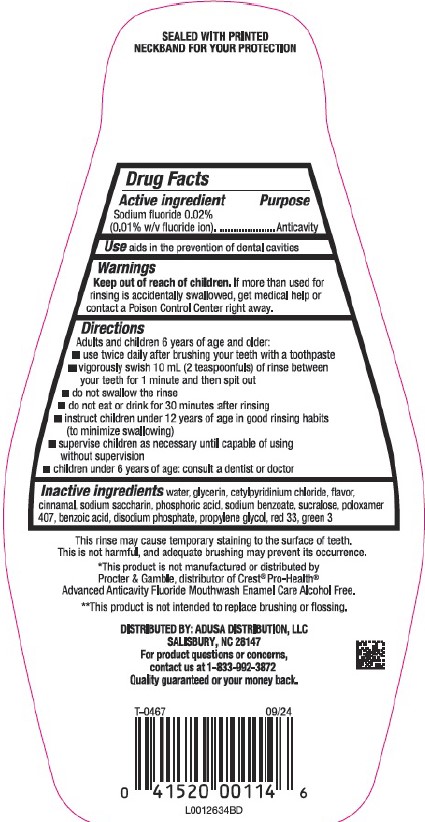 DRUG LABEL: Alcohol-Free Anticavity
NDC: 72476-482 | Form: LIQUID
Manufacturer: Retail Business Services, LLC
Category: otc | Type: HUMAN OTC DRUG LABEL
Date: 20260206

ACTIVE INGREDIENTS: SODIUM FLUORIDE 0.1 mg/1 mL
INACTIVE INGREDIENTS: GLYCERIN; CETYLPYRIDINIUM CHLORIDE; CINNAMALDEHYDE; SACCHARIN SODIUM; PHOSPHORIC ACID; SODIUM BENZOATE; SUCRALOSE; POLOXAMER 407; BENZOIC ACID; SODIUM PHOSPHATE, DIBASIC, ANHYDROUS; PROPYLENE GLYCOL; D&C RED NO. 33; WATER; FD&C GREEN NO. 3

Care One 482.002/482AC
Alcohol Free Fluoride Violet Mint Mouthwash

TEP

SEALED WITH PRINTED NECKBAND FOR YOUR PROTECTION

Active ingredient

Sodium fluoride 0.02% (0.01% w/v fluoride ion)

Purpose

Anticavity

Use

aids in the prevention of dental cavities

Warnings

for this product

Keep out of reach of children.

If more than used for rinsing is accidentally swallowed, get medical help or contact a Poison Control Center right away.

Directions

Adults and children 6 years of age and older:

- use twice daily after brushing your teeth with a toothpaste
- vigorously swish 10 mL (2 teaspoonfuls) of rinse between your teeth for 1 minute and then spit out
- do not swallow the rinse
- do not eat or drink for 30 minutes after rinsing
- instruct children under 12 years of age in good rinsing habits (to minimize swallowing)
- supervise children as necessary until capable of using without supervision
- children under 6 years of age: consult a dentist or doctor

Inactive ingredients

water, glycerin, cetylpyridinium chloride, flavor, cinnamal, sodium saccharin, phosphoric acid, sodium benzoate, sucralose, poloxamer 407, benzoic acid, disodium phosphate, propylene glycol, red 33, green 3

Disclaimer

This rinse may cause temporary staining to the surface of teeth.

This is not harmful, and adequate brushing may prevent its occurrence.

*This product is not manufactured or distributed by Procter & Gamble, distributor of Crest®Pro-Health® Advanced Anticavity Flouride Mouthwash Enamel Care Alcohol Free.

**This product is not intended to replace brushing or flossing.

Adverse reaction

DISTRIBUTED BY: ADUSA DISTRIBUTION, LLC

SALISBURY, NC 28147

For product questions or concerns, contact us at 1-833-992-3872

Quality guaranteed or your money back.

Principal display panel

CAREONE®

Compare to the Active Ingredient in Crest®Pro-Health®Advanced Anticavity Fluoride Mouthwash*

ALCOHOL FREE

FLUORIDE MOUTHWASH

ANTICAVITY

FLUORIDE RINSE

VIOLET MINT FLAVOR

KILLS BAD BREATH GERMS

HELPS PREVENT CAVITIES

HELPS STRENGTHEN ENAMEL

CLEANS TEETH**

FRESHENS BREATH

IMPORTANT: Read directions for proper use

33.8 FL OZ (1.05 QT) 1L